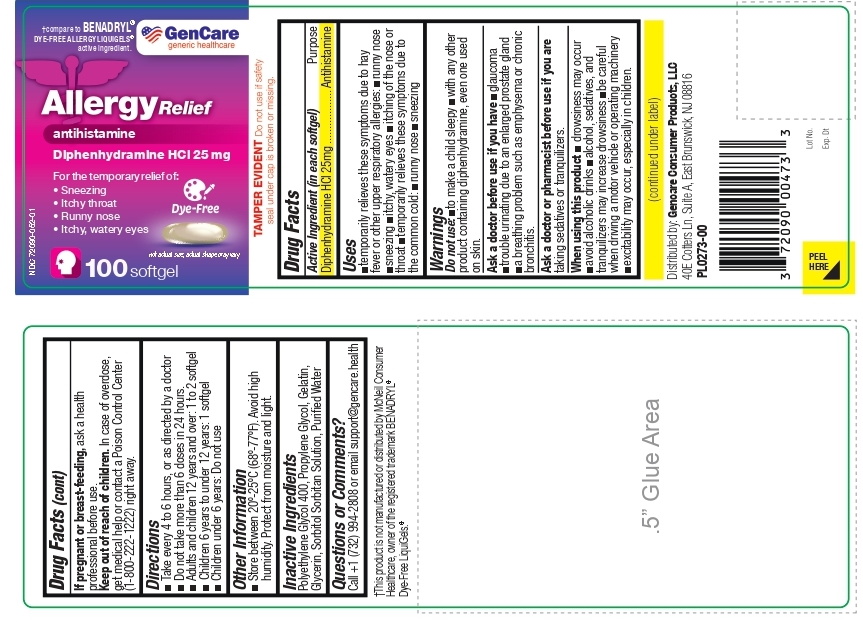 DRUG LABEL: Allergy Relief Diphenhydramine HCl 25mg SoftGel
NDC: 72090-052 | Form: CAPSULE, LIQUID FILLED
Manufacturer: Pioneer Life Sciences, LLC
Category: otc | Type: HUMAN OTC DRUG LABEL
Date: 20250630

ACTIVE INGREDIENTS: DIPHENHYDRAMINE HYDROCHLORIDE 25 mg/1 1
INACTIVE INGREDIENTS: POLYETHYLENE GLYCOL 400; PROPYLENE GLYCOL; Gelatin; Glycerin; SORBITOL SOLUTION; Sorbitan; WATER

Gencare-Allergy Relief Diphenhydramine HCl 25mg SoftGel

Active Ingredient (In Each Softgel)

Diphenhydramine HCl 25mg

Purpose

Antihistamine

Uses

■temporarily relieves these symptoms due to hay fever or other upper respiratory allergies: ■runny nose ■sneezing ■itchy, watery eyes ■itching of the nose or throat ■temporarily relieves these symptoms due to the common cold: ■runny nose ■sneezing

Warnings

Do not use:

■ to make a child sleepy

■ with any other product containing diphenhydramine, even one used on skin.

Ask a doctor before use if you have

■ glaucoma
■ trouble urinating due to an enlarged prostate gland
■ a breathing problem such as emphysema or chronic bronchitis.

Ask a doctor or pharmacist before use if you are taking sedatives or tranquilizers.

When using this product

■ drowsiness may occur
■ avoid alcoholic drinks
■ alcohol, sedatives, and tranquilizers may increase drowsiness
■ be careful when driving a motor vehicle or operating machinery
■ excitability may occur, especially in children.

PREGNANCY OR BREAST FEEDING

If pregnant or breast-feeding, ask a health professional before use.

Keep out of reach of children. In case of overdose, get medical help or contact a Poison Control Center (1-800-222-1222) right away.

Directions:

■ Take every 4 to 6 hours, or as directed by a doctor
■ Do not take more than 6 doses in 24 hours.
■ Adults and children 12 years and over: 1 to 2 softgels
■ Children 6 years to under 12 years: 1 softgel
■ Children under 6 years: Do not use

Other Information:

■ Store between 20º-25ºC (68º-77ºF). Avoid high humidity. Protect from moisture and light.

Inactive Ingredients:

Polyethylene Glycol 400, Propylene Glycol, Gelatin, Glycerin, Sorbitol Sorbitan Solution, Purified Water

Questions Or Comments?

Call +1 (732) 994-2808 or email support@gencare.health